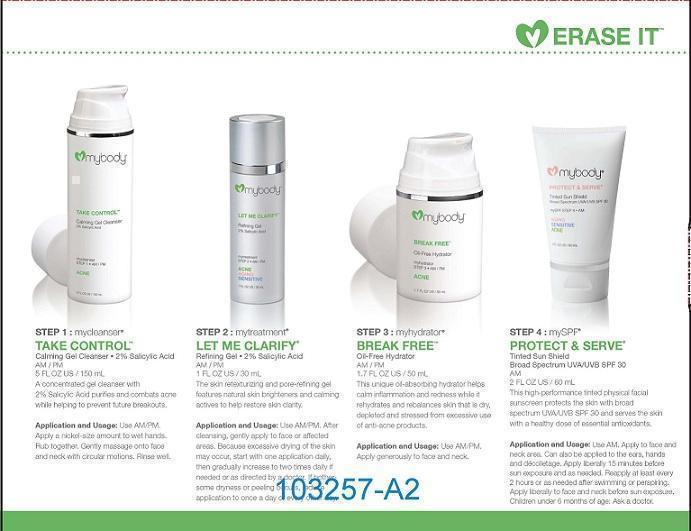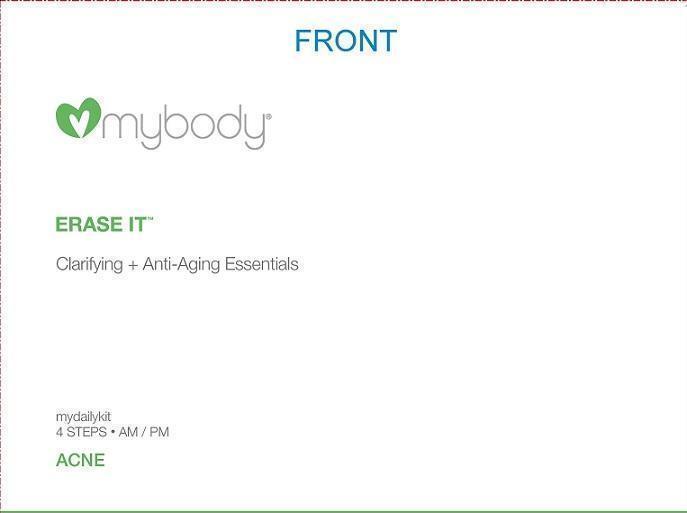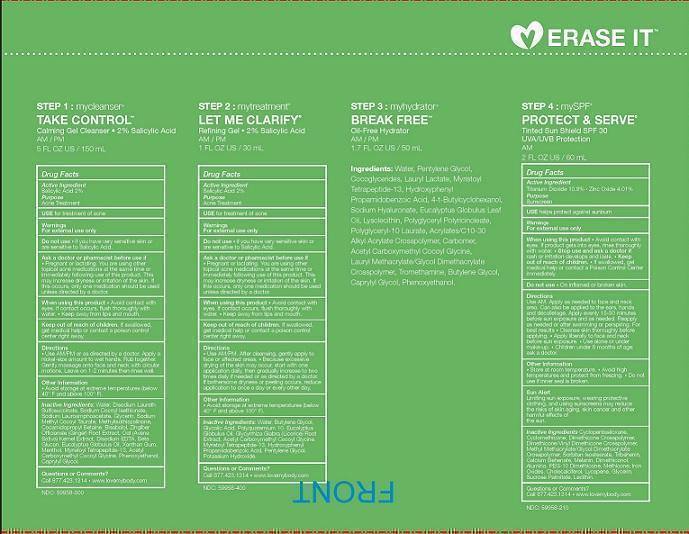 DRUG LABEL: ERASE IT KIT
NDC: 49520-501 | Form: KIT | Route: TOPICAL
Manufacturer: mybody
Category: otc | Type: HUMAN OTC DRUG LABEL
Date: 20140628

ACTIVE INGREDIENTS: TITANIUM DIOXIDE 11 g/100 mL; ZINC OXIDE 4 g/100 mL; SALICYLIC ACID 2 g/100 mL; SALICYLIC ACID 2 g/100 mL
INACTIVE INGREDIENTS: CYCLOMETHICONE 5; CYCLOMETHICONE; DIMETHICONE/VINYL DIMETHICONE CROSSPOLYMER (SOFT PARTICLE); METHYL METHACRYLATE/GLYCOL DIMETHACRYLATE CROSSPOLYMER; SORBITAN ISOSTEARATE; TRIBEHENIN; CALCIUM BEHENATE; MELANIN SYNTHETIC (TYROSINE, PEROXIDE); DIMETHICONOL (41 MPA.S); ALUMINUM OXIDE; PEG-10 DIMETHICONE (600 CST); METHICONE (20 CST); FERRIC OXIDE RED; CHOLECALCIFEROL; LYCOPENE; GLYCERIN; SUCROSE PALMITATE; LECITHIN, SOYBEAN; WATER; DISODIUM LAURETH SULFOSUCCINATE; SODIUM COCOYL ISETHIONATE; SODIUM LAUROAMPHOACETATE; GLYCERIN; SODIUM METHYL COCOYL TAURATE; METHYLISOTHIAZOLINONE; COCAMIDOPROPYL BETAINE; .ALPHA.-BISABOLOL, (+/-)-; GINGER; OAT; EDETATE DISODIUM; CURDLAN; EUCALYPTUS OIL; XANTHAN GUM; MENTHOL; MYRISTOYL PENTAPEPTIDE-4; ACETYL CARBOXYMETHYL COCOYL GLYCINE; PHENOXYETHANOL; CAPRYLYL GLYCOL; WATER; 1,3-BUTYLENE GLYCOL; GLYCOLIC ACID; POLYQUATERNIUM-10 (400 CPS AT 2%); EUCALYPTUS GLOBULUS LEAF; GLYCYRRHIZA GLABRA; ACETYL CARBOXYMETHYL COCOYL GLYCINE; MYRISTOYL TETRAPEPTIDE-4; HYDROXYPHENYL PROPAMIDOBENZOIC ACID; PENTYLENE GLYCOL; POTASSIUM HYDROXIDE

ACTIVE INGREDIENT

SALICYLIC ACID 2%

PURPOSE

ACNE TREATMENT

INDICATIONS AND USAGE

USE FOR TREATMENT OF ACNE

WARNINGS

FOR EXTERNAL USE ONLY

DO NOT USE * IF YOU HAVE VERY SENSITIVE SKIN OR ARE SENSITIVE TO SALICYLIC ACID.

ASK A DOCTOR OR PHARMACIST BEFORE USE IF *PREGNANT OR LACTATING. YOU ARE USING OTHER TOPICAL ACNE MEDICATIONS AT THE SAME TIME OR IMMEDIATELY FOLLOWING USE OF THIS PRODUCT. THIS MAY INCREASE DRYNESS OR IRRITATION OF THE SKIN. IF THIS OCCURS, ONLY ONE MEDICATION SHOULD BE USED UNLESS DIRECTED BY A DOCTOR.

WHEN USING THIS PRODUCT * AVOID CONTACT WITH EYES. IF CONTACT OCCURS, FLUSH THOROUGHLY WITH WATER. * KEEP AWAY FROM LIPS AND MOUTH.

KEEP OUT OF REACH OF CHILDREN. IF SWALLOWED, GET MEDICAL HELP OR CONTACT A POISON CONTROL CENTER RIGHT AWAY.

DIRECTIONS

* USE AM/PM OR AS DIRECTED BY A DOCTOR. APPLY A NICKEL-SIZE AMOUNT TO WET HANDS. RUB TOGETHER. GENTLY MASSAGE ONTO FACE AND NECK WITH CIRCULAR MOTIONS. LEAVE ON 1-2 MINUTES THEN RINSE WELL.

OTHER INFORMATION

* AVOID STORAGE AT EXTREME TEMPERATURES (BELOW 40°F AND ABOVE 100°F).

INACTIVE INGREDIENT

INACTIVE INGREDIENTS: WATER, DISODIUM LAURETH SULFOSUCCINATE, SODIUM COCOYL ISETHIONATE, SODIUM LAUROAMPHOACETATE, GLYCERIN, SODIUM METHYL COCOYL TAURATE, METHYLISOTHIAZOLINONE, COCAMIDOPROPYL BETAINE, BISABOLOL, ZINGIBER OFFICINALE (GINGER) ROOT EXTRACT, OAT (AVENA SATIVA) KERNEL EXTRACT, DISODIUM EDTA, BETA GLUCAN, EUCALYPTUS GLOBULUS OIL, XANTHAN GUM, MENTHOL, MYRISTOYL TETRAPEPTIDE-13, ACETYL CARBOXYMETHYL COCOYL GLYCINE, PHENOXYETHANOL, CAPRYLYL GLYCOL.

QUESTIONS OR COMMENTS?

CALL 877.423.1314 * WWW.LOVEMYBODY.COM